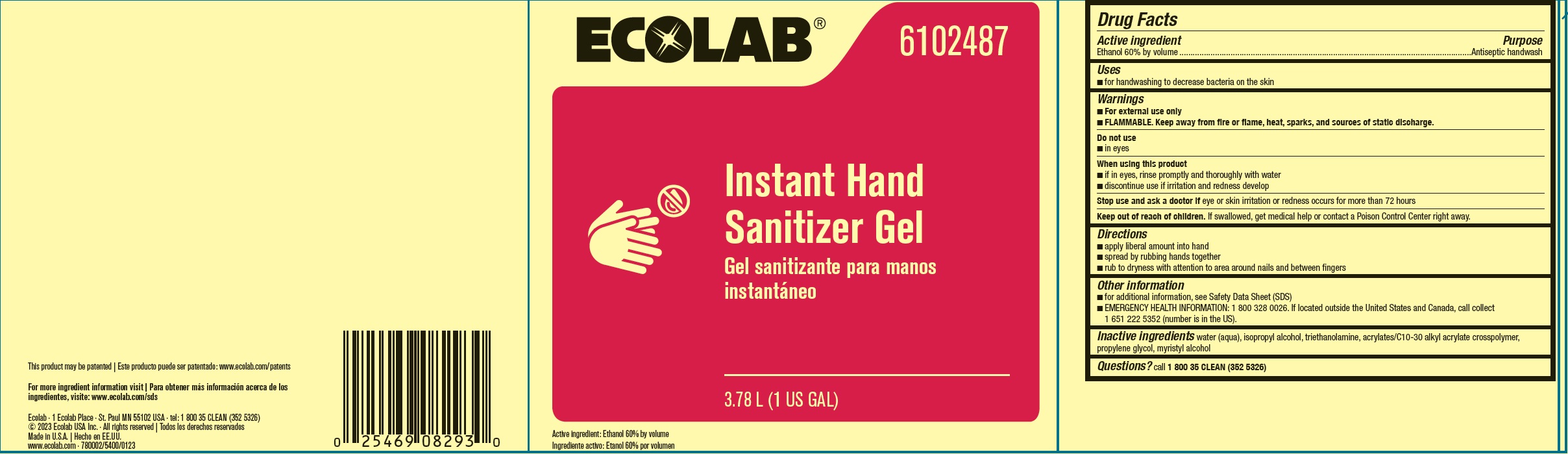 DRUG LABEL: Ecolab
NDC: 47593-507 | Form: LIQUID
Manufacturer: Ecolab Inc.
Category: otc | Type: HUMAN OTC DRUG LABEL
Date: 20251230

ACTIVE INGREDIENTS: ALCOHOL 60 mL/100 mL
INACTIVE INGREDIENTS: WATER; ISOPROPYL ALCOHOL; TROLAMINE; CARBOMER COPOLYMER TYPE B (ALLYL PENTAERYTHRITOL CROSSLINKED); PROPYLENE GLYCOL; MYRISTYL ALCOHOL

Drug Facts

Active ingredient

Ethanol 60% by volume

Purpose

Antispetic handwash

Uses

- For handwashing to decrease bacteria on the skin

Warnings

- For external use only
- FLAMMABLE, keep away from fire or flame, heat, sparks and sources of static discharge

Do not use

- In eyes

When using this product

- If in eyes, rinse promptly and thoroughly with water
- Discontinue use if irritation and rendess develop

Stop use and ask a doctor if eye or skin irritation or redenss occurs for more than 72 hours

Keep out of reach of children. If swallowed, get medical help or contact a Poison Control Center right away.

Directions

- Apply liberal amount into hand
- Spread by rubbing hands together
- Rub to dryness with attention to are around nails and between fingers

Other information

- For additional information, see Safety Data Sheet (SDS)
- EMERGENCY HEALTH INFORMATION: 1 800 328 0026. If located outside the United States and Canada, call collect 1 651 222 5352 (number is in the US).

INACTIVE INGREDIENT

Inactive ingredients water (aqua), isopropyl alcohol, triethanolamine, acrylates/C10-30 alkyl acrylate crosspolymer, propylene glycol, myristyl alcohol

Questions? call 1-800-35-CLEAN (352-5326)

Principal Display Panel and Representative Label

ECOLAB®

6102487

Instant Hand

Sanitizer Gel

3.78 L (1 US GAL)

Active Ingredient: Ethanol 60% by volume

Ecolab · 1 Ecolab Place · St. Paul MN 55102 USA · tel: 1 800 35 CLEAN (352 5326)

© 2023 Ecolab USA Inc. · All rights reserved

Made in U.S.A.

www.ecolab.com · 780002/5400/0123